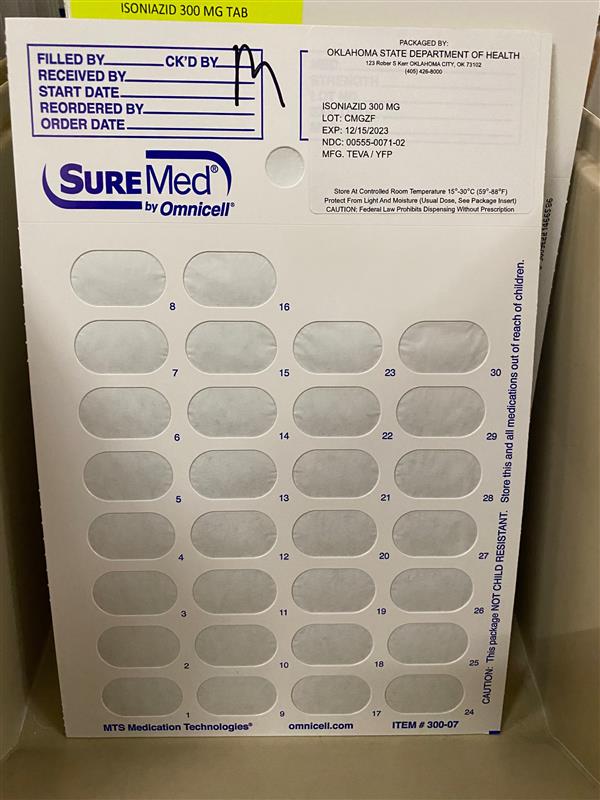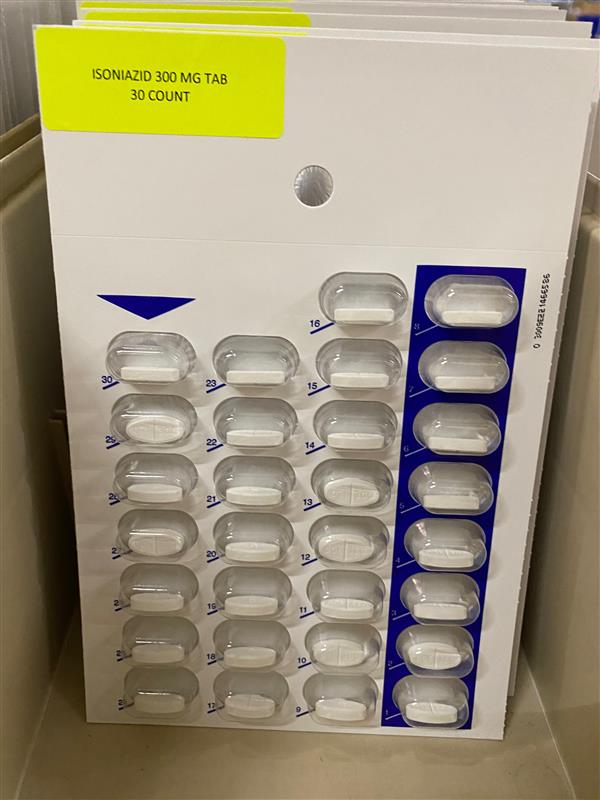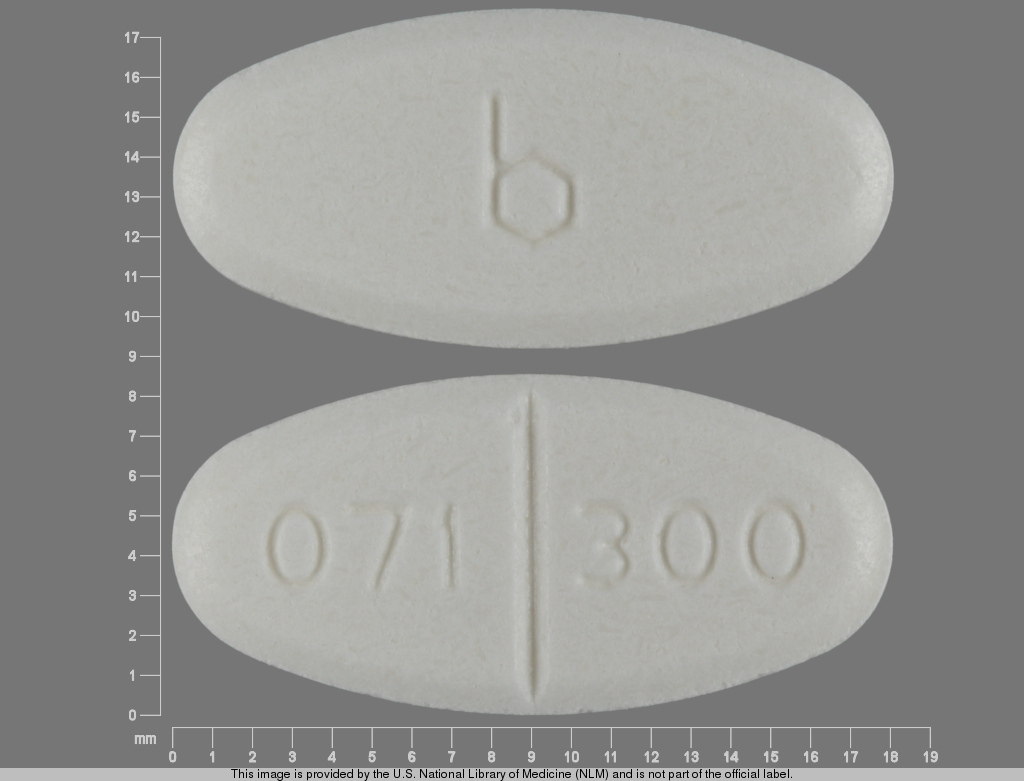 DRUG LABEL: Isoniazid 300 mg
NDC: 83112-071 | Form: TABLET
Manufacturer: Health Department, Oklahoma State
Category: prescription | Type: HUMAN PRESCRIPTION DRUG LABEL
Date: 20230208

ACTIVE INGREDIENTS: ISONIAZID 300 mg/1 1

Isoniazid 300 mg

Dosing and Administration

For Treatment of Tuberculosis

Isoniazid is used in conjunction with other effective anti-tuberculous agents. Drug susceptibility testing should be performed on the organisms initially isolated from all patients with newly diagnosed tuberculosis. If the bacilli becomes resistant, therapy must be changed to agents to which the bacilli are susceptible.

Usual Oral Dosage (depending on the regimen used):

Adults

5 mg/kg up to 300 mg daily in a single dose; or

15 mg/kg up to 900 mg/day, two or three times/week

Children

10 mg/kg to 15 mg/kg up to 300 mg daily in a single dose; or

20 mg/kg to 40 mg/kg up to 900 mg/day, two or three times/week

Patients with Pulmonary Tuberculosis Without HIV Infection

There are 3 regimen options for the initial treatment of tuberculosis in children and adults:

Option 1

Daily isoniazid, rifampin and pyrazinamide for 8 weeks followed by 16 weeks of isoniazid and rifampin daily or 2 to 3 times weekly. Ethambutol or streptomycin should be added to the initial regimen until sensitivity to isoniazid and rifampin is demonstrated. The addition of a fourth drug is optional if the relative prevalence of isoniazid-resistant Mycobacterium tuberculosis isolates in the community is less than or equal to four percent.

Option 2

Daily isoniazid, rifampin, pyrazinamide and streptomycin or ethambutol for 2 weeks followed by twice weekly administration of the same drugs for 6 weeks, subsequently twice weekly isoniazid and rifampin for 16 weeks.

Option 3

Three times weekly with isoniazid, rifampin, pyrazinamide and ethambutol or streptomycin for 6 months.

*All regimens given twice weekly or 3 times weekly should be administered by directly observed therapy

[see also Directly Observed Therapy (DOT)].

The above treatment guidelines apply only when the disease is caused by organisms that are susceptible to the standard antituberculous agents. Because of the impact of resistance to isoniazid and rifampin on the response to therapy, it is essential that physicians initiating therapy for tuberculosis be familiar with the prevalence of drug resistance in their communities. It is suggested that ethambutol not be used in children whose visual acuity cannot be monitored.

Patients with Pulmonary Tuberculosis and HIV Infection

The response of the immunologically impaired host to treatment may not be as satisfactory as that of a person with normal host responsiveness. For this reason, therapeutic decisions for the impaired host must be individualized. Since patients co-infected with HIV may have problems with malabsorption, screening of antimycobacterial drug levels, especially in patients with advanced HIV disease, may be necessary to prevent the emergence of MDRTB.

Patients with Extra Pulmonary Tuberculosis

The basic principles that underlie the treatment of pulmonary tuberculosis also apply to extra pulmonary forms of the disease. Although there have not been the same kinds of carefully conducted controlled trials of treatment of extra pulmonary tuberculosis as for pulmonary disease, increasing clinical experience indicates that a 6 to 9 month short-course regimen is effective. Because of the insufficient data, miliary tuberculosis, bone/joint tuberculosis and tuberculous meningitis in infants and children should receive 12 month therapy.

Bacteriologic evaluation of extra pulmonary tuberculosis may be limited by the relative inaccessibility of the sites of disease. Thus, response to treatment often must be judged on the basis of clinical and radiographic findings.

The use of adjunctive therapies such as surgery and corticosteroids is more commonly required in extra pulmonary tuberculosis than in pulmonary disease. Surgery may be necessary to obtain specimens for diagnosis and to treat such processes as constrictive pericarditis and spinal cord compression from Pott’s Disease. Corticosteroids have been shown to be of benefit in preventing cardiac constriction from tuberculous pericarditis and in decreasing the neurologic sequelae of all stages of tuberculosis meningitis, especially when administered early in the course of the disease.

Pregnant Women with Tuberculosis

The options listed above must be adjusted for the pregnant patient. Streptomycin interferes with in utero development of the ear and may cause congenital deafness. Routine use of pyrazinamide is also not recommended in pregnancy because of inadequate teratogenicity data. The initial treatment regimen should consist of isoniazid and rifampin. Ethambutol should be included unless primary isoniazid resistance is unlikely (isoniazid resistance rate documented to be less than 4%).

Treatment of Patients with Multi-Drug Resistant Tuberculosis (MDRTB)

Multiple-drug resistant tuberculosis (i.e., resistance to at least isoniazid and rifampin) presents difficult treatment problems. Treatment must be individualized and based on susceptibility studies. In such cases, consultation with an expert in tuberculosis is recommended.

Directly Observed Therapy (DOT)

A major cause of drug-resistant tuberculosis is patient noncompliance with treatment. The use of DOT can help assure patient compliance with drug therapy. DOT is the observation of the patient by a health care provider or other responsible person as the patient ingests anti-tuberculosis medications. DOT can be achieved with daily, twice weekly or thrice weekly regimens and is recommended for all patients.

For Preventative Therapy of Tuberculosis

Before isoniazid preventive therapy is initiated, bacteriologically positive or radiographically progressive tuberculosis must be excluded. Appropriate evaluations should be performed if extra pulmonary tuberculosis is suspected.

Adults over 30 kg: 300 mg per day in a single dose.

Infants and Children: 10 mg/kg (up to 300 mg daily) in a single dose. In situations where adherence with daily preventative therapy cannot be assured, 20 mg/kg to 30 mg/kg (not to exceed 900 mg) twice weekly under the direct observation of a health care worker at the time of administration8.

Continuous administration of isoniazid for a sufficient period is an essential part of the regimen because relapse rates are higher if chemotherapy is stopped prematurely. In the treatment of tuberculosis, resistant organisms may multiply and the emergence of resistant organisms during the treatment may necessitate a change in the regimen.

For following patient compliance: the Potts-Cozart test9, a simple colorimetric6 method of checking for isoniazid in the urine, is a useful tool for assuring patient compliance, which is essential for effective tuberculosis control. Additionally, isoniazid test strips are also available to check patient compliance.

Concomitant administration of pyridoxine (B6) is recommended in the malnourished and in those predisposed to neuropathy (e.g., alcoholics and diabetics).